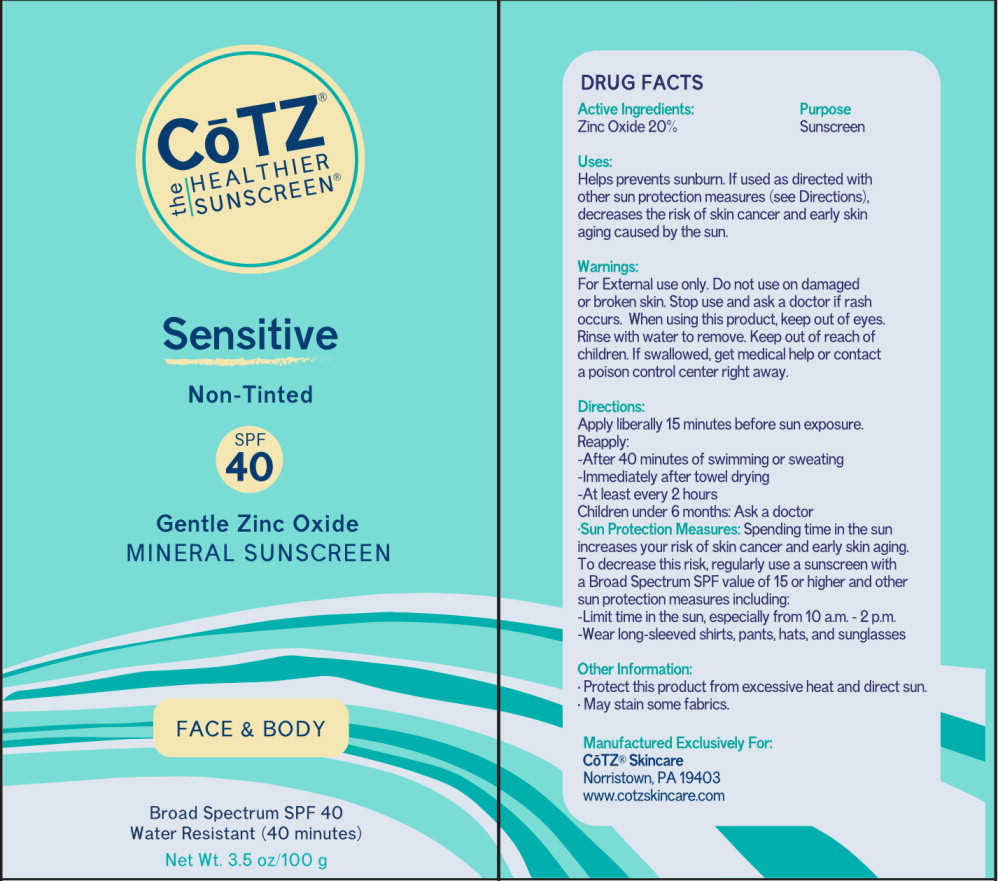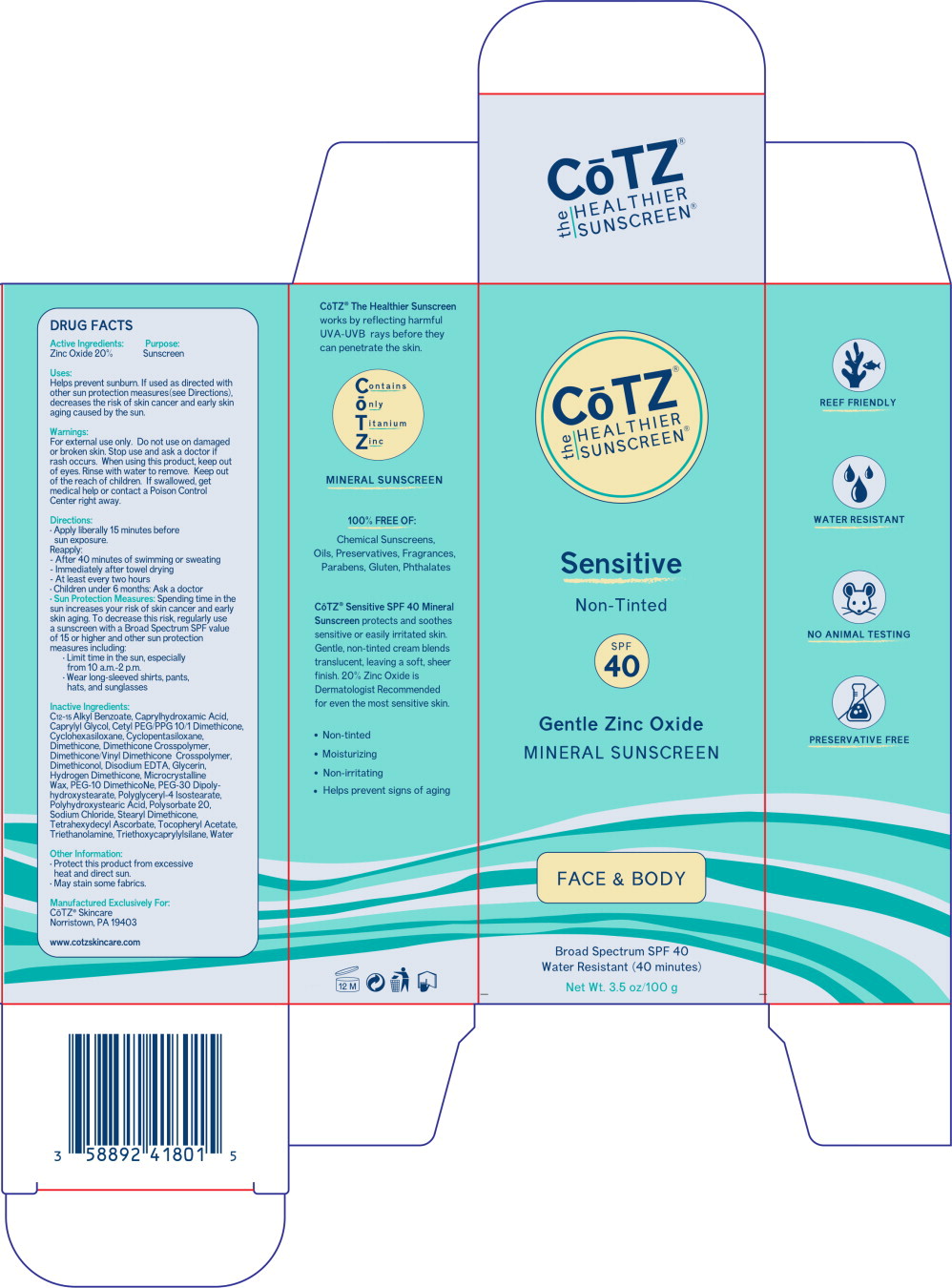 DRUG LABEL: Cotz Sensitive SPF 40 
NDC: 58892-418 | Form: LOTION
Manufacturer: Fallien Cosmeceuticals, LTD.
Category: otc | Type: HUMAN OTC DRUG LABEL
Date: 20250331

ACTIVE INGREDIENTS: Zinc Oxide 200 mg/1 g
INACTIVE INGREDIENTS: Alkyl (C12-15) Benzoate; Caprylhydroxamic Acid; Caprylyl Glycol; Cetyl PEG/PPG-10/1 Dimethicone (HLB 5); Cyclomethicone 6; Cyclomethicone 5; Dimethicone 100; Dimethicone/Diene Dimethicone Crosspolymer; Edetate Disodium; Methicone (20 cst); Microcrystalline Wax; PEG-10 Dimethicone (600 cst); PEG-30 Dipolyhydroxystearate; Polyglyceryl-4 Isostearate; Polyhydroxystearic Acid (2300 MW); Polysorbate 20; Sodium Chloride; Stearyl Dimethicone (400 MPA.S AT 50C); Tetrahexyldecyl Ascorbate; .Alpha.-Tocopherol Acetate; Trolamine; Triethoxycaprylylsilane; Water

Active Ingredients:

Zinc Oxide 20%

Purpose:

Sunscreen

Uses:

Helps prevent sunburn. If used as directed with other sun protection measures (see Directions), decreases the risk of skin cancer and early skin aging caused by the sun.

Warnings:

DO NOT USE

For external use only. Do not use on damaged or broken skin.

Stop use and ask a doctor if rash occurs.

When using this product, keep out of eyes. Rinse with water to remove.

KEEP OUT OF REACH OF CHILDREN

Keep out of the reach of children. If swallowed, get medical help or contact a Poison Control Center right away.

Directions:

- Apply liberally 15 minutes before sun exposure.
  Reapply:
  - After 40 minutes of swimming or sweating
  - Immediately after towel drying
  - At least every two hours
- Children under 6 months: Ask a doctor
- Sun Protection Measures: Spending time in the sun increases your risk of skin cancer and early skin aging. To decrease this risk, regularly use a sunscreen with a Broad Spectrum SPF value of 15 or higher and other sun protection measures including:
  - Limit time in the sun, especially from 10 a.m.-2 p.m.
  - Wear long-sleeved shirts, pants, hats, and sunglasses

Inactive Ingredients:

C12-15 Alkyl Benzoate, Caprylhydroxamic Acid, Caprylyl Glycol, Cetyl PEG/PPG10/1 Dimethicone, Cyclohexasiloxane, Cyclopentasiloxane, Dimethicone, Dimethicone Crosspolymer, Dimethicone/Vinyl Dimethicone Crosspolymer, Dimethiconol, Disodium EDTA, Glycerin, Hydrogen Dimethicone, Microcrystalline Wax, PEG-10 Dimethicone, PEG-30 Dipolyhydroxystearate, Polyglyceryl-4 Isostearate, Polyhydroxystearic Acid, Polysorbate 20, Sodium Chloride, Stearyl Dimethicone, Tetrahexydecyl Ascorbate, Tocopheryl Acetate, Triethanolamine, Triethoxycaprylylsilane, Water

Other Information:

- Protect this product from excessive heat and direct sun.
- May stain some fabrics.

Manufactured Exclusively For:

CoTZ® Skincare
Norristown, PA 19403

www.cotzskincare.com

Principal Display Panel – CoTZ Sensitive Tube Label

CoTZ®

the HEALTHIER
SUNSCREEN®

Sensitive

Non-Tinted

SPF
40

Gentle Zinc Oxide

MINERAL SUNSCREEN

FACE & BODY

Broad Spectrum SPF 40

Water Resistant (40 minutes)

Net Wt. 3.5 oz/100 g

Principal Display Panel – CoTZ Sensitive Carton Label

CoTZ®

the HEALTHIER
SUNSCREEN®

Sensitive

Non-Tinted

SPF
40

Gentle Zinc Oxide

MINERAL SUNSCREEN

FACE & BODY

Broad Spectrum SPF 40

Water Resistant (40 minutes)

Net Wt. 3.5 oz/100 g